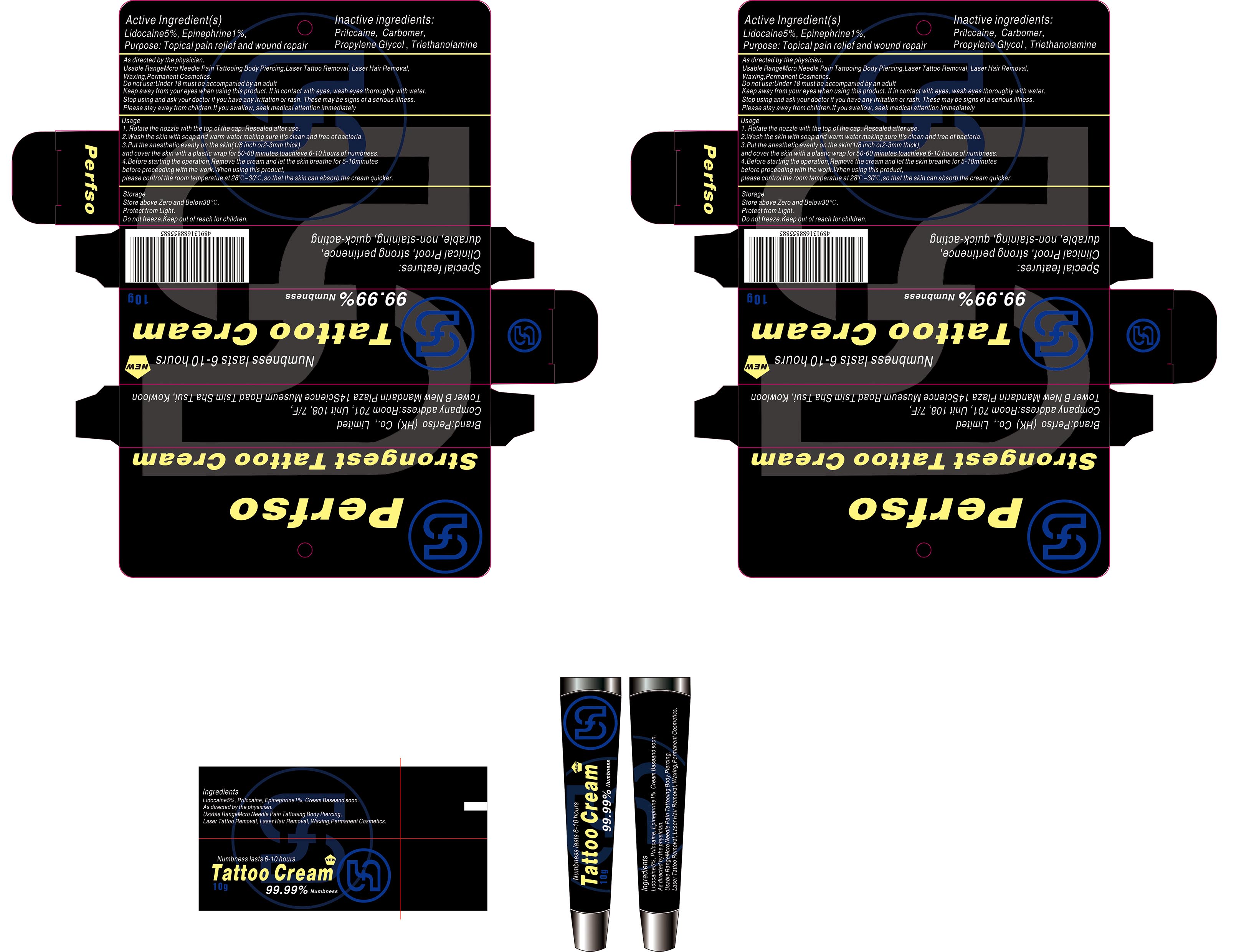 DRUG LABEL: Tattoo
NDC: 85942-001 | Form: CREAM
Manufacturer: Perfso (HK) Co., Limited
Category: otc | Type: HUMAN OTC DRUG LABEL
Date: 20250708

ACTIVE INGREDIENTS: LIDOCAINE 5 g/100 g; EPINEPHRINE 1 g/100 g
INACTIVE INGREDIENTS: PROPYLENE GLYCOL; CARBOMER; PROCAINE; TRIETHANOLAMINE

ACTIVE INGREDIENT

Lidocaine 5%, Epinephrine 1%

PURPOSE

Topical pain relief and wound repair

INDICATIONS AND USAGE

As directed by the physician.

Usable RangeMcro Needle Pain Tattooing Body Piercing,Laser Tattoo Removal, Laser Hair Removal, Waxing,Permanent Cosmetics.

WARNINGS

n/a

Do not use:Under 18 must be accompanied by an adult

WHEN USING

Keep away from your eyes when using this product. If in contact with eyes, wash eyes thoroughly with water.

STOP USE

Stop using and ask your doctor if you have any irritation or rash. These may be signs of a serious illness.

Please stay away from children.If you swallow, seek medical attention immediately

Keep out of reach for children.

DOSAGE AND ADMINISTRATION

Usage

1. Rotate the nozzle with the top of the cap. Resealed after use.

2.Wash the skin with soap and warm water making sure It's clean and free of bacteria.

3.Put the anesthetic evenly on the skin(1/8 inch or2-3mm thick), and cover the skin with a plastic wrap for 50-60 minutes toachieve 6-10 hours of numbness.

4.Before starting the operation,Remove the cream and let the skin breathe for 5-10minutes before proceeding with the work.When using this product, please control the room temperatue at 28C ~30C,so that the skin can absorb the cream quicker.

Storage

Store above Zero and Below30°℃.

Protect from Light.

Do not freeze.

INACTIVE INGREDIENT

Prilccaine, Carbomer, Propylene Glycol, Triethanolamine